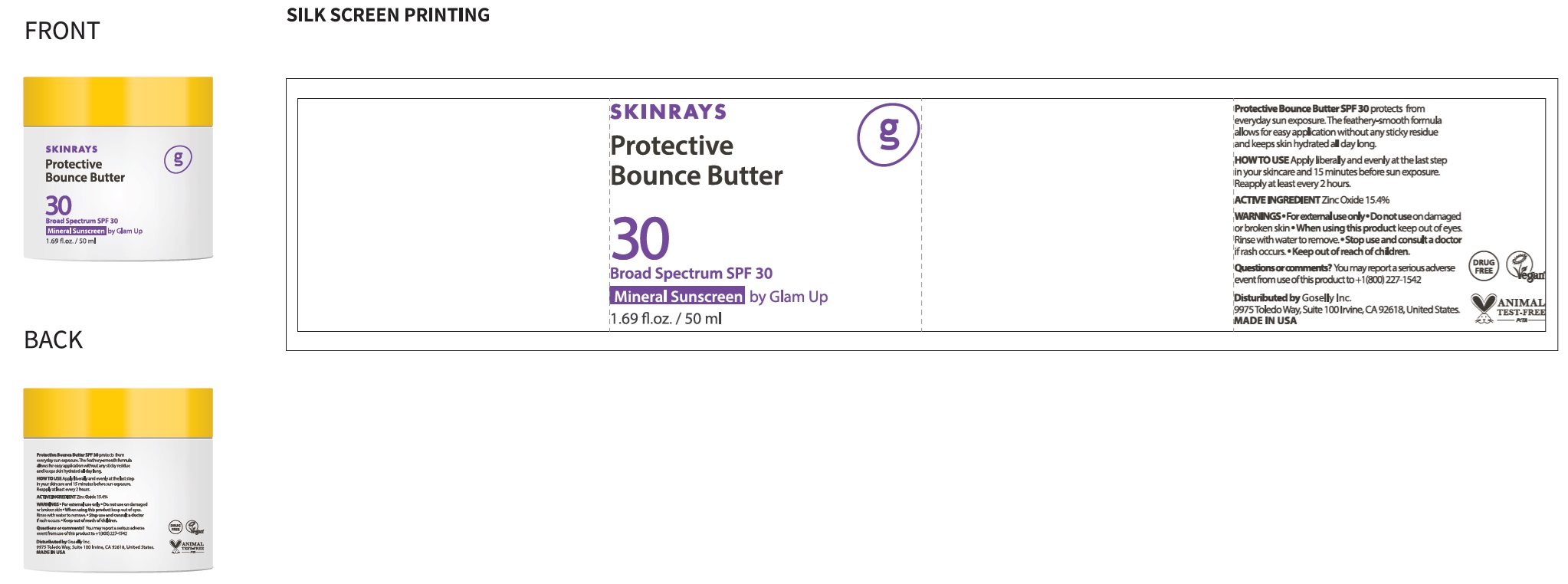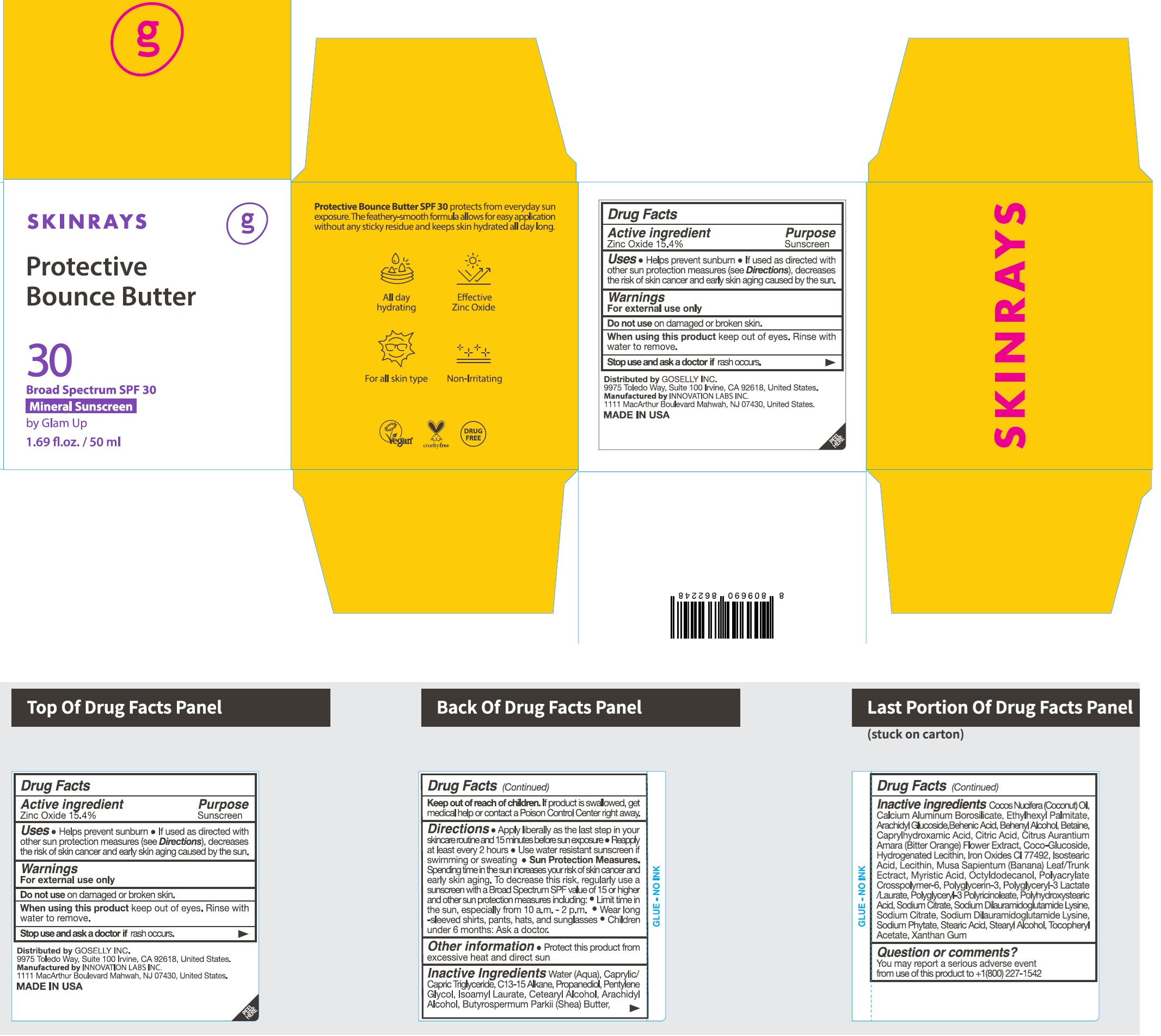 DRUG LABEL: SKINRAYS Protective Bounce Butter Broad Spectrum SPF 30 Mineral Sunscreen by Glam up
NDC: 84656-530 | Form: CREAM
Manufacturer: Spigen Beauty Inc.
Category: otc | Type: HUMAN OTC DRUG LABEL
Date: 20240814

ACTIVE INGREDIENTS: ZINC OXIDE 154 mg/1 mL
INACTIVE INGREDIENTS: WATER; MEDIUM-CHAIN TRIGLYCERIDES; C13-15 ALKANE; PROPANEDIOL; PENTYLENE GLYCOL; ISOAMYL LAURATE; CETOSTEARYL ALCOHOL; ARACHIDYL ALCOHOL; SHEA BUTTER; COCONUT OIL; CALCIUM ALUMINUM BOROSILICATE; ETHYLHEXYL PALMITATE; ARACHIDYL GLUCOSIDE; BEHENIC ACID; DOCOSANOL; BETAINE; CAPRYLHYDROXAMIC ACID; CITRIC ACID MONOHYDRATE; CITRUS AURANTIUM FLOWER; COCO-GLUCOSIDE; FERRIC OXIDE RED; FERRIC OXIDE YELLOW; ISOSTEARIC ACID; BANANA; MYRISTIC ACID; OCTYLDODECANOL; SODIUM CITRATE, UNSPECIFIED FORM; SODIUM DILAURAMIDOGLUTAMIDE LYSINE; PHYTATE SODIUM; STEARIC ACID; STEARYL ALCOHOL; .ALPHA.-TOCOPHEROL ACETATE; XANTHAN GUM

SKINRAYS. Protective Bounce Butter Broad Spectrum SPF 30 Mineral Sunscreen by Glam up

Active ingredient

Zinc Oxide 15.4%

Purpose

Sunscreen

Uses

- Helps prevent sunburn
- If used as directed with other sun protection measures (see Directions), decreases the risk of skin cancer and early skin aging caused by the sun.

Warnings

For external use only

Do not use

on damaged or broken skin.

When using this product

keep out of eyes. Rinse with water to remove.

Stop use and ask a doctor if

rash occurs.

Keep out of reach of children.

If product is swallowed, get medical help or contact a Poison Control Center right away.

Directions

- Apply liberally as the last step in your skincare routine and 15 minutes before sun exposure
- Reapply at least every 2 hours
- Use water resistant sunscreen if swimming or sweating
- Sun Protection Measures.Spending time in the sun increases your risk of skin cancer and early skin aging. To decrease this risk, regularly use a sunscreen with a Broad Spectrum SPF value of 15 or higher and other sun protection measures including:
- Limit time in the sun, especially from 10 a.m. - 2 p.m.
- Wear long -sleeved shirts, pants, hats, and sunglasses
- Children under 6 months: Ask a doctor.

Other information

- Protect this product from excessive heat and direct sun

Inactive Ingredients

Water (Aqua), Caprylic/Capric Triglyceride, C13-15 Alkane, Propanediol, Pentylene Glycol, Isoamyl Laurate, Cetearyl Alcohol, Arachidyl Alcohol, Butyrospermum Parkii (Shea) Butter, Cocos Nucifera (Coconut) Oil, Calcium Aluminum Borosilicate, Ethylhexyl Palmitate, Arachidyl Glucoside,Behenic Acid, Behenyl Alcohol, Betaine, Caprylhydroxamic Acid, Citric Acid, Citrus Aurantium Amara (Bitter Orange) Flower Extract, Coco-Glucoside, Hydrogenated Lecithin, Iron Oxides CI 77492, Isostearic Acid, Lecithin, Musa Sapientum (Banana) Leaf/Trunk Ectract, Myristic Acid, Octyldodecanol, Polyhydroxystearic Acid, Sodium Citrate, Sodium Dilauramidoglutamide Lysine, Sodium Citrate, Sodium Dilauramidoglutamide Lysine, Sodium Phytate, Stearic Acid, Stearyl Alcohol, Tocopheryl Acetate, Xanthan Gum

Question or comments?

You may report a serious Adverse event from use of this product to + 1(800) 227-1542